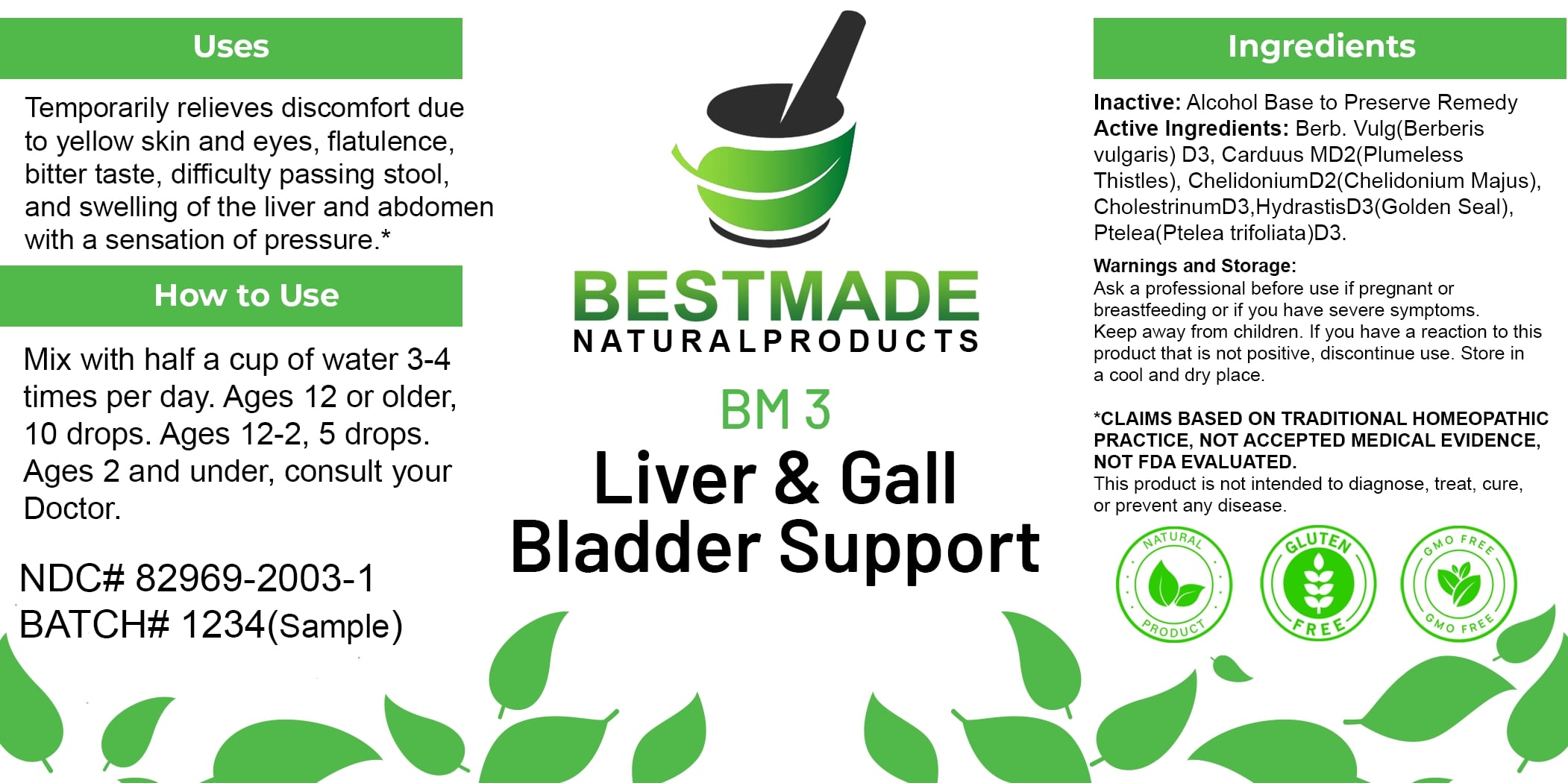 DRUG LABEL: Bestmade Natural Products BM3
NDC: 82969-2003 | Form: LIQUID
Manufacturer: Bestmade Natural Products
Category: homeopathic | Type: HUMAN OTC DRUG LABEL
Date: 20250122

ACTIVE INGREDIENTS: CHELIDONIUM MAJUS 30 [hp_C]/30 [hp_C]; CHOLESTEROL 30 [hp_C]/30 [hp_C]; PTELEA TRIFOLIATA BARK 30 [hp_C]/30 [hp_C]; SILYBUM MARIANUM SEED 30 [hp_C]/30 [hp_C]; GOLDENSEAL 30 [hp_C]/30 [hp_C]; BERBERIS VULGARIS ROOT BARK 30 [hp_C]/30 [hp_C]
INACTIVE INGREDIENTS: ALCOHOL 30 [hp_C]/30 [hp_C]

BM3

DOSAGE AND ADMINISTRATION

How to Use
Mix with half a cup of water 3-4 times per day. Ages 12 or older, 10 drops. Ages 12-2, 5 drops. Ages 2 and under, consult your Doctor.

Inactive:

Alcohol Base to Preserve Product

INDICATIONS AND USAGE

Temporarily relieves discomfort due to yellow skin and eyes, flatulence, bitter taste, difficulty passing stool, and swelling of the liver and abdomen with a sensation of pressure.*

*Claims Based on Traditional Homeopathic Practice, Not Accepted Medical Evidence, Not FDA Evaluated.
This product is not intended to diagnose, treat, cure, or prevent any disease.

Active Ingredients:

Berb. Vulg (Berberis vulgaris) D3, Carduus MD2 (Plumeless Thistles), ChelidoniumD2 (Chelidonium Majus), CholesterniumD3, HydrastisD3 (Golden Seal), Ptelea (Ptelea trifoliata) D3.

KEEP OUT OF REACH OF CHILDREN

Warnings and Storage:
Ask a professional before use if pregnant or breastfeeding or if you have severe symptoms. Keep away from children. If you have a reaction to this product that is not positive, discontinue use. Store in a cool and dry place.

PURPOSE

Temporarily relieves discomfort due to yellow skin and eyes, flatulence, bitter taste, difficulty passing stool, and swelling of the liver and abdomen with a sensation of pressure.*

*Claims Based on Traditional Homeopathic Practice, Not Accepted Medical Evidence, Not FDA Evaluated.
This product is not intended to diagnose, treat, cure, or prevent any disease.

Warnings and Storage:
Ask a professional before use if pregnant or breastfeeding or if you have severe symptoms. Keep away from children. If you have a reaction to this product that is not positive, discontinue use. Store in a cool and dry place.

Claims Based on Traditional Homeopathic Practice, Not Accepted Medical Evidence, Not FDA Evaluated.
This product is not intended to diagnose, treat, cure, or prevent any disease.

Entire package label